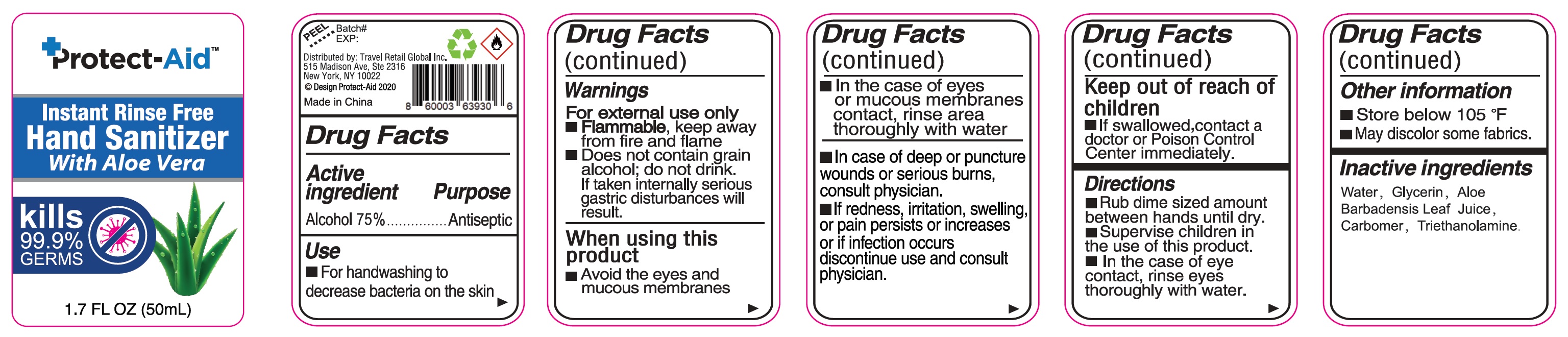 DRUG LABEL: Hand Sanitizer
NDC: 77129-001 | Form: GEL
Manufacturer: Travel Retail Global Inc.
Category: otc | Type: HUMAN OTC DRUG LABEL
Date: 20231031

ACTIVE INGREDIENTS: ALCOHOL 0.75 mL/1 mL
INACTIVE INGREDIENTS: WATER; GLYCERIN; ALOE VERA LEAF; CARBOMER HOMOPOLYMER, UNSPECIFIED TYPE; TROLAMINE

Hand Sanitizer

Active ingredient

Alcohol 75%

Purpose

Antiseptic

Use

- For handwashing to decrease bacteria on the skin

Warnings

For external use only.

- Keep away from fire and flame Flammable,
- Does not contain grain alcohol; do not drink. If taken internally serious gastric disturbances will result.

When using this product

- Avoid the eyes and mucous membrances
- In the case of eyes or mucous membranes contact, rinse area thoroughly with water
- In case of deep or puncture wounds or serious burns, consult physician.
- If redness, irritation, swelling, or pain persists or increases or if infection occurs discontinue use and consult physician.

Keep out of reach of children.

- If swallowed,contact a doctor or Poison Control Center immediately.

Directions

- Rub drime sized amount between hands until dry.
- Supervise children in the use of this product.
- In the case of eye contact, rinse eyes thoroughly with water.

Other information

- Store below 105 °F
- May discolor some fabrics.

Inactive ingredients

Water, Glycerin, Aloe Barbadensis Leaf Juice, Carbomer, Triethanolamine.